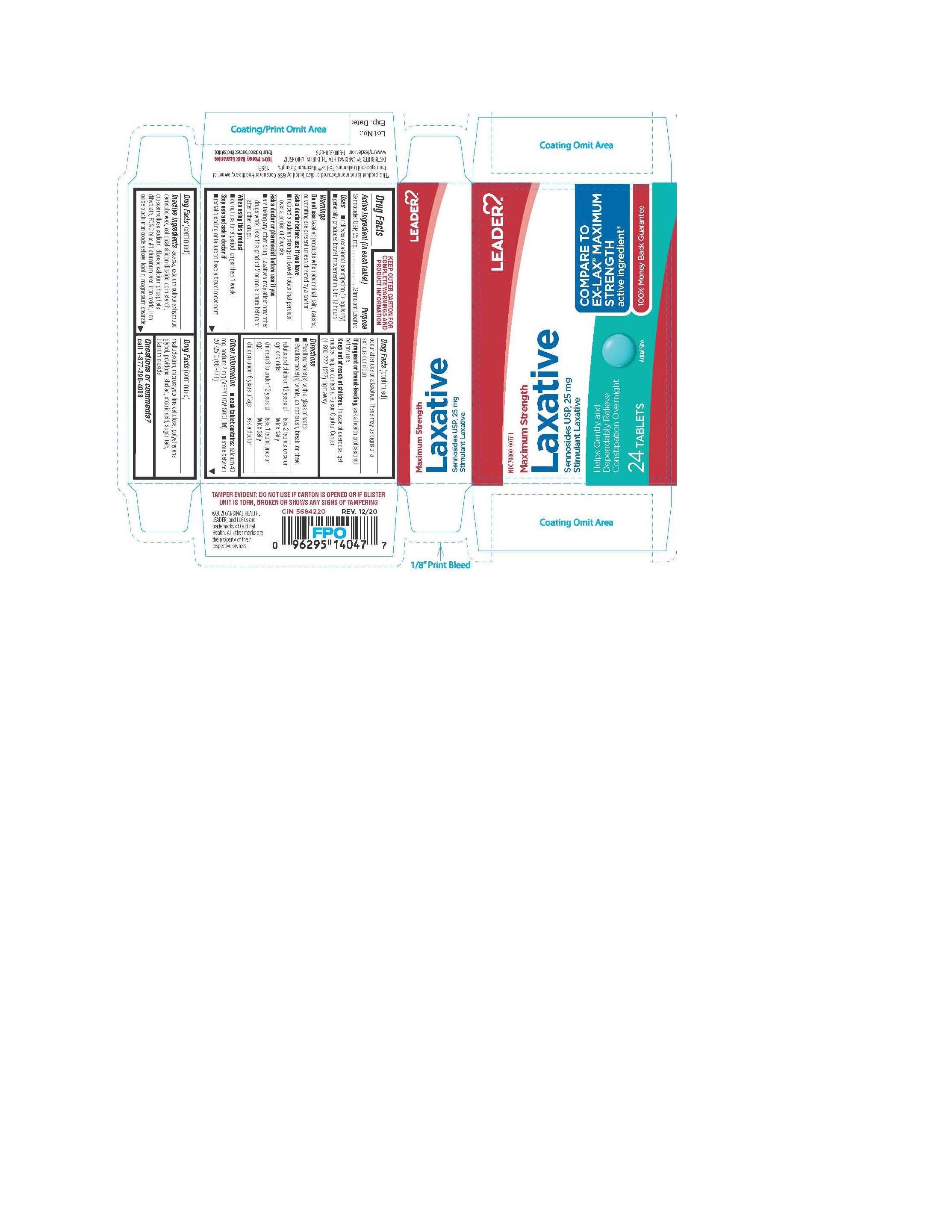 DRUG LABEL: MAXIMUM STRENGTH LAXATIVE
NDC: 70000-0077 | Form: TABLET
Manufacturer: CARDINAL HEALTH
Category: otc | Type: HUMAN OTC DRUG LABEL
Date: 20240110

ACTIVE INGREDIENTS: SENNOSIDES 25 mg/1 1
INACTIVE INGREDIENTS: CROSCARMELLOSE; FERROUS OXIDE; FD&C BLUE NO. 1; FERRIC OXIDE YELLOW; MAGNESIUM STEARATE; POLYETHYLENE GLYCOL, UNSPECIFIED; POVIDONE; DIBASIC CALCIUM PHOSPHATE DIHYDRATE; KAOLIN; RAW SUGAR; ACACIA; FERROSOFERRIC OXIDE; STEARIC ACID; MALTODEXTRIN; CARNAUBA WAX; STARCH, CORN; CALCIUM SULFATE ANHYDROUS; SILICON DIOXIDE; MICROCRYSTALLINE CELLULOSE; SHELLAC; TALC; TITANIUM DIOXIDE

195R LEADER-CARDINAL 24 COUNT BLISTERS 70000-0077-1

ACTIVE INGREDIENT

Each Tablet contains:

SENNOSIDES,USP 25 mg

INACTIVE INGREDIENTS

INACTIVE INGREDIENTS: acacia, calcium sulfate anhydrous, carnauba wax, colloidal silicon dioxide, corn starch, croscarmellose sodium, dibasic calcium phosphate dihydrate, FD&C blue#1, iron oxide, iron oxide black, iron oxide yellow, kaolin, magnesium stearate, maltodextrin, microcrystalline cellulose, polyethylene glycol, povidone, shellac, stearic acid, sugar, talc, titanium dioxide

PURPOSE:

Stimulant Laxative

Keep out of Reach of Children: In case of overdose, get medical help or contact a Poison Control Center right away.

INDICATIONS & USAGE

Uses:

Relieves occasional constipation (irregularity); generally causes bowel movement in 6-12 hours

WARNINGS:

Do not use this product
If you are presently taking mineral oil, unless directed by a doctor
Laxative products for longer than 1 week unless directed by a doctor

Directions:

Swallow tablet(s) with a glass of water

Swallow tablet(s) whole do not crush, break, or chew

Adults and children 12years of age and older | Take 2 tablets once or twice daily
Children 6 to under 12 years of age | Take 1 tablet once or twice daily
children under 6 years of age | ask a doctor